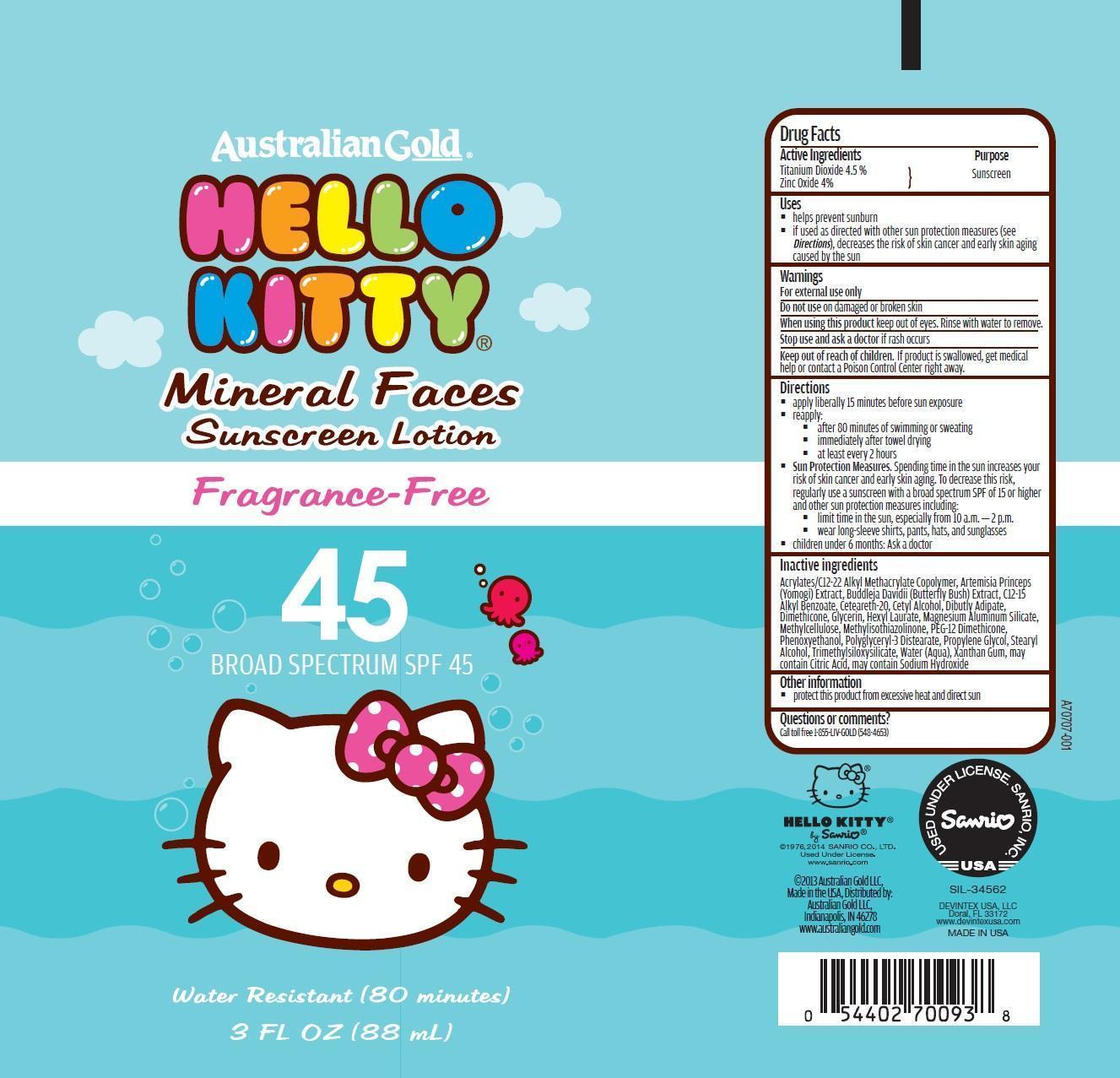 DRUG LABEL: Australian Gold
NDC: 58443-0219 | Form: LOTION
Manufacturer: Prime Enterprises Inc.
Category: otc | Type: HUMAN OTC DRUG LABEL
Date: 20200117

ACTIVE INGREDIENTS: ZINC OXIDE 41.6 mg/1 mL; TITANIUM DIOXIDE 46.8 mg/1 mL
INACTIVE INGREDIENTS: POLYGLYCERYL-3 DISTEARATE; XANTHAN GUM; BUTYL ACRYLATE/C16-C20 ALKYL METHACRYLATE/METHACRYLIC ACID/METHYL METHACRYLATE COPOLYMER; CITRIC ACID MONOHYDRATE; ALKYL (C12-15) BENZOATE; CETEARETH-22; CETYL ALCOHOL; PHENOXYETHANOL; PROPYLENE GLYCOL; DIMETHICONE; TRIMETHYLSILOXYSILICATE (M/Q 0.8-1.0); GLYCERIN; HEXYL LAURATE; MAGNESIUM ALUMINUM SILICATE; METHYLCELLULOSE (100 CPS); WATER; PEG-12 DIMETHICONE (300 CST); TRIETHOXYCAPRYLYLSILANE; ALUMINUM HYDROXIDE; STEARIC ACID; BUDDLEJA DAVIDII LEAF; ARTEMISIA PRINCEPS LEAF OIL; SODIUM HYDROXIDE; STEARYL ALCOHOL; DIBUTYL ADIPATE; METHYLISOTHIAZOLINONE

Australian Gold Hello Kitty Mineral Faces Suncreen

Active Ingredients

Titanium Dioxide 4.5%

Zinc Oxide 4%

Purpose

Sunscreen

Uses

- helps prevent sunburn
- if used as directed with other sun protection measures (see Directions), decreases the risk of skin cancer and early skin aging caused by the sun.

WARNINGS

For external use only.

Do not use on damaged or broken skin

When using this product keep out of eyes. Rinse with water to remove.

Stop use and ask a doctor if rash occurs

Keep out of reach of children. If product is swallowed, get medical help or contact a Poison Control Center right away.

Directions

- apply liberally 15 minutes before sun exposure
- reapply:
- after 80 minutes of swimming or sweating
- immediately after towel drying
- at least every 2 hours
- Sun Protection Measures. Spending time in the sun increases your risk of skin cancer and early skin aging. To decrease this risk, regularly use a sunscreen with Broad Spectrum SPF of 15 or higher and other sun protection measures including:
- limit time in the sun, especially from 10 a.m. – 2 p.m.
- wear long-sleeve shirts, pants, hats, and sunglasses
- children under 6 months: Ask a doctor

INACTIVE INGREDIENT

Acrylates/C12-22 Alkyl Methacrylate Copolymer, Aluminum Hydroxide, Artemisia Princeps (Yomogi) Extract, Buddleja Davidii (Butterfly Bush) Extract, C12-15 Alkyl Benzoate, Ceteareth-20, Cetyl Alcohol, Dibutly Adipate, Dimethicone, Glycerin, Hexyl Laurate, Magnesium Aluminum Silicate, Methylcellulose, Methylisothiazolinone, PEG-12 Dimethicone, Phenoxyethanol, Polyglyceryl-3 Distearate, Propylene Glycol, Stearic Acid, Stearyl Alcohol, Triethoxycaprylylsilane, Trimethylsiloxysilicate, Water (Aqua), Xanthan Gum, may contain Citric Acid, may contain Sodium Hydroxide

Other Information

- protect this product from excessive heat and direct sun

Questions or Comments?

Call toll free 1-855-LIV-GOLD (548-4653)